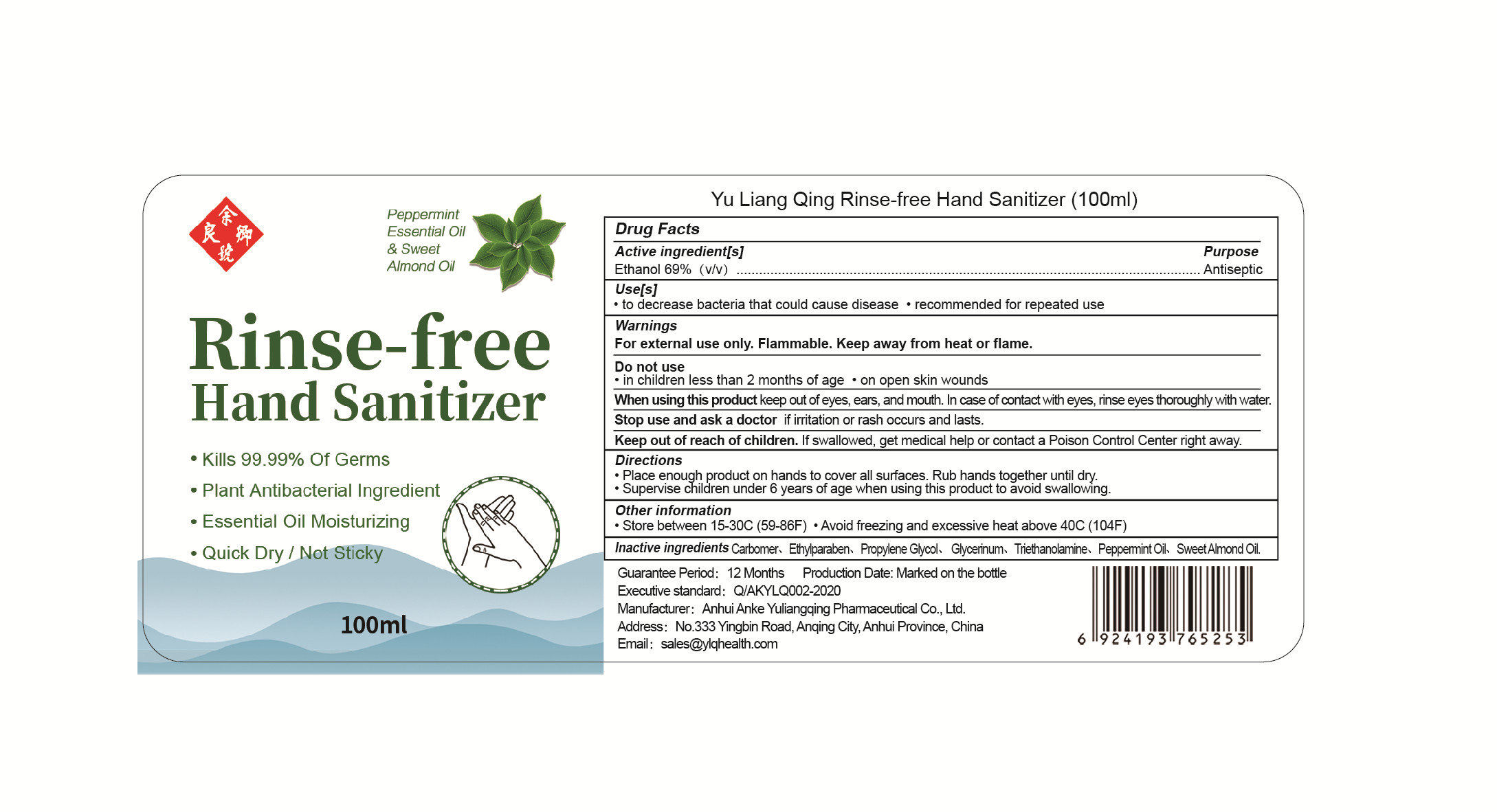 DRUG LABEL: Rinse-free Hand Sanitizer
NDC: 53168-001 | Form: LIQUID
Manufacturer: Anhui Anke Yuliangqing Pharmaceutical Co., Ltd.
Category: otc | Type: HUMAN OTC DRUG LABEL
Date: 20200510

ACTIVE INGREDIENTS: ALCOHOL 69 mL/100 mL
INACTIVE INGREDIENTS: GLYCERIN; POLYACRYLIC ACID (250000 MW); ETHYLPARABEN; PROPYLENE GLYCOL; PEPPERMINT OIL; TROLAMINE; ALMOND OIL

DOSAGE AND ADMINISTRATION

Keep away from heat or flame.Store between 15-30°C (59-86F)

INACTIVE INGREDIENT

Carbomer

Ethylparaben

Propylene Glycol

Glycerinum

Triethanolamine

Peppermint Oil

Sweet Almond Oil

INDICATIONS AND USAGE

●Place enough product on hands to cover all surfaces. Rub hands together until dry.
●Supervise children under 6 years of age when using this product to avoid swallowing.

ACTIVE INGREDIENT

Ethanol

keep out of reach of children

PURPOSE

Disinfection
Sterilization
No Rinseing

WARNINGS

For external use only. Flammable. Keep away from heat or flame.